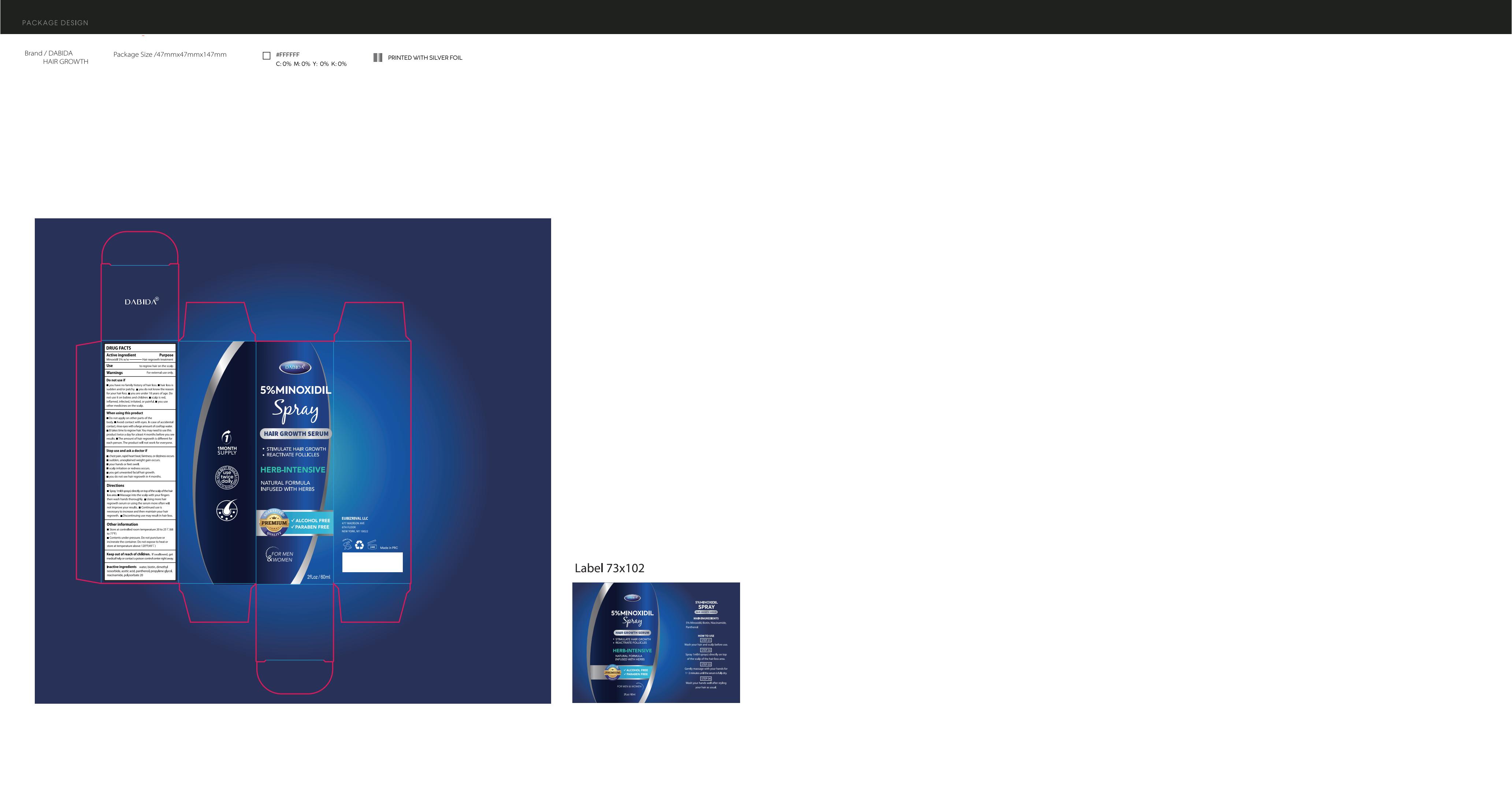 DRUG LABEL: 5% Minoxidil hair growth oil
NDC: 83462-005 | Form: LIQUID
Manufacturer: Eubizrival LLC
Category: otc | Type: HUMAN OTC DRUG LABEL
Date: 20231102

ACTIVE INGREDIENTS: MINOXIDIL 5 g/100 mL
INACTIVE INGREDIENTS: PROPYLENE GLYCOL; POLYSORBATE 20; WATER; ACETIC ACID; DIMETHYL ISOSORBIDE; PANTHENOL; NIACINAMIDE; BIOTIN

Active Ingredient

Minoxidil 5% w/w

Purpose

Hair regrowth treatment

Use

to regrow hair on the scalp

Warnings

For external use only.

Do not use

You have no family history of hair loss. Hair loss is sudden and/or patchy. You do not know the reason for your hair loss. You are under 18 years of age. Do not use it on babies and children.Scalp is red, inflamed, infected, irritated or painful.You use other medicines on the scalp.

When Using

Do not apply on other parts of the body. Avoid contact with eyes. In case of accidental contact, rinse eyes with a large amount of cool tap water. It takes time to regrow hair. You may need to use this product 2 times a day for at least 4 months before you see results, The amount of hair regrowth is different for each person.The product will not work for everyone.

Stop Use

If scalp irritation or redness occurs. If you get unwanted facial hair growth. If you do not see hair regrowth in 4 months.If sudden, unexplained weight gain occurs.

Ask Doctor

If you have chest pain, rapid heart beat, faintness,
or dizziness occurs.

Keep Oot Of Reach Of Children

If swallowed, get medical help or contact
a poison control center right away.

Directions

. Apply 2-3 drops of serum directly to the
scalp in the area to be treated.
. Massage into the scalp with your fingers
then wash hands thoroughly.
- Using more hair regrowth serum or
using the serum more often will not
improve your results.
. Continued use is necessary to increase
and then maintain your hair regrowth.
. Discontinuing use may result in hair loss.

Other information

Before use, read all information on the carton.
Keep the carton. It contains important
information.
Store at controlled room temperature 20
to 25℃ (68 to 77°F)
Contents under pressure. Do not
puncture or incinerate the container. Do
not expose to heat or store at
temperature above 120°F(49℃)

Inactive ingredients

water, biotin, dimethyl isosorbide,
acetic acid, panthenol, propylene glycol,
niacinamide, polysorbate 20